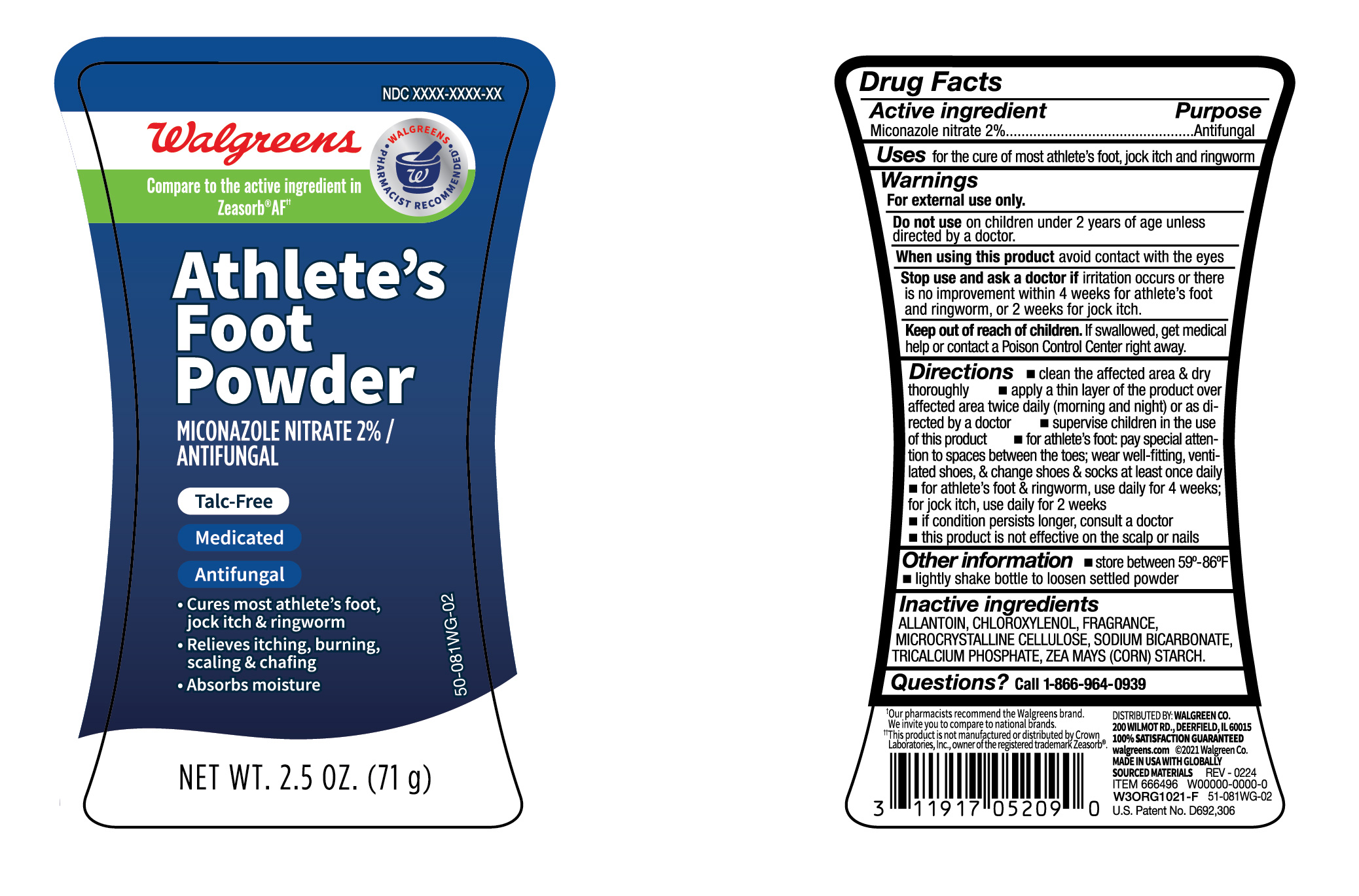 DRUG LABEL: Foot Powder
NDC: 0363-7999 | Form: POWDER
Manufacturer: Walgreens Company
Category: otc | Type: HUMAN OTC DRUG LABEL
Date: 20260128

ACTIVE INGREDIENTS: MICONAZOLE NITRATE 20 mg/1 g
INACTIVE INGREDIENTS: ALLANTOIN; CHLOROXYLENOL; SODIUM BICARBONATE; TRICALCIUM PHOSPHATE; MICROCRYSTALLINE CELLULOSE; STARCH, CORN

Walgreens Athlete's Foot Powder

Active ingredient

Miconazole nitrate 2%

Purpose

Antifungal

Uses

for the cure of most athlete's foot, jock itch and ringworm

Warnings

For external use only.

Do not use

on children 2 years of age unless directed by a doctor.

When using this product

avoid contact with the eyes

Stop and ask a doctor if

irritation occurs or there is no improvement within 4 weeks for athlete's foot and ringworm, or 2 weeks for jock itch.

Keep out of reach of children.

If swallowed, get medical help or contact a Poison Control Center right away.

Directions

- clean the affected area and dry thoroughly
- apply a thin layer of product over affected area twice daily (morning and night) or as directed by a doctor
- supervise children in the use of this product
- for athlete's foot: pay special attention to spaces between the toes; wear well-fitting, ventilated shoes, and change shoes and socks at least once daily
- for athlete's foot and ringworm, use daily for 4 weeks; for jock itch, use daily for 2 weeks
- if conditions persist longer, consult a doctor
- this product is not effective on the scalp or nails

Other information

- store between 59º - 86ºF
- lightly shake bottle to loosen settled powder

Inactive ingredients

allantoin, chloroxylenol, fragrance, microcrystalline cellulose, sodium bicarbonate, tricalcium phosphate, zea mays (corn) starch

Questions?

call 1-866-964-0939

Principal Display Panel

Walgreens

Athlete's

Foot

Powder

MICONAZOLE NITRATE 2%/ANTIFUNGAL

- Talc-Free
- Medicated
- Antifungal
- Cures most athlete's foot, jock itch & ringworm
- Relieves itching, burning, scaling & chafing
- Absorbs moisture

NET WT. 2.5 OZ. (71 g)